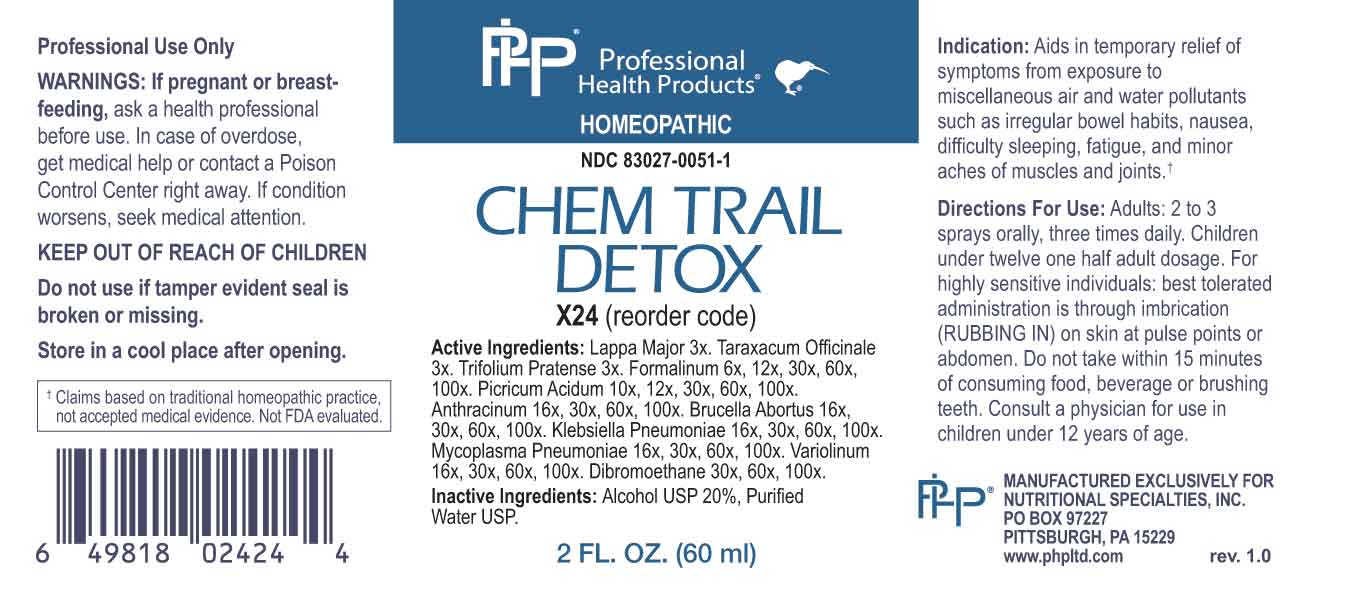 DRUG LABEL: Chem Trail Detox
NDC: 83027-0051 | Form: SPRAY
Manufacturer: Nutritional Specialties, Inc.
Category: homeopathic | Type: HUMAN OTC DRUG LABEL
Date: 20240814

ACTIVE INGREDIENTS: ARCTIUM LAPPA ROOT 3 [hp_X]/1 mL; TARAXACUM OFFICINALE 3 [hp_X]/1 mL; TRIFOLIUM PRATENSE FLOWER 3 [hp_X]/1 mL; FORMALDEHYDE SOLUTION 6 [hp_X]/1 mL; PICRIC ACID 10 [hp_X]/1 mL; BACILLUS ANTHRACIS IMMUNOSERUM RABBIT 16 [hp_X]/1 mL; BRUCELLA ABORTUS 16 [hp_X]/1 mL; KLEBSIELLA PNEUMONIAE 16 [hp_X]/1 mL; MYCOPLASMA PNEUMONIAE 16 [hp_X]/1 mL; VACCINIA VIRUS 16 [hp_X]/1 mL; ETHYLENE DIBROMIDE 30 [hp_X]/1 mL
INACTIVE INGREDIENTS: WATER; ALCOHOL

DRUG FACTS:

ACTIVE INGREDIENTS:

Lappa Major 3X, Taraxacum Officinale 3X, Trifolium Pratense 3X, Formalinum 6X, 12X, 30X, 60X, 100X, Picricum Acidum 10X, 12X, 30X, 60X, 100X, Anthracinum 16X, 30X, 60X, 100X, Brucella Abortus 16X, 30X, 60X, 100X, Klebsiella Pneumoniae 16X, 30X, 60X, 100X, Mycoplasma Pneumoniae 16X, 30X, 60X, 100X, Variolinum 16X, 30X, 60X, 100X, Dibromoethane 30X, 60X, 100X.

PURPOSE:

Aids in temporary relief of symptoms from exposure to miscellaneous air and water pollutants such as irregular bowel habits, nausea, difficulty sleeping, fatigue, and minor aches of muscles and joints.†

†Claims based on traditional homeopathic practice, not accepted medical evidence. Not FDA evaluated.

WARNINGS:

Professional Use Only

If pregnant or breast-feeding, ask a health professional before use.

In case of overdose, get medical help or contact a Poison Control Center right away.

If condition worsens, seek medical attention.

KEEP OUT OF REACH OF CHILDREN

Do not use if tamper evident seal is broken or missing.

Store in a cool place after opening

KEEP OUT OF REACH OF CHILDREN:

In case of overdose, get medical help or contact a Poison Control Center right away.

DIRECTIONS:

Adults: 2 to 3 sprays orally, three times daily. Children under twelve one half adult dosage. For highly sensitive individuals: best tolerated administration is through imbrication (RUBBING IN) on skin at pulse points or abdomen. Do not take within 15 minutes of consuming food, beverage or brushing teeth. Consult a physician for use in children under 12 years of age.

INDICATIONS:

Aids in temporary relief of symptoms from exposure to miscellaneous air and water pollutants such as irregular bowel habits, nausea, difficulty sleeping, fatigue, and minor aches of muscles and joints.†

†Claims based on traditional homeopathic practice, not accepted medical evidence. Not FDA evaluated.

INACTIVE INGREDIENTS:

Alcohol USP 20%, Purified Water USP.

QUESTIONS:

MANUFACTURED EXCLUSIVELY FOR

NUTRITIONAL SPECIALTIES, INC.

PO BOX 97227

PITTSBURG, PA 15229

www.phpltd.com

PACKAGE LABEL DISPLAY:

Professional

Health Products

HOMEOPATHIC

NDC 83027-0051-1

CHEM TRAIL

DETOX

2 FL. OZ (60 ml)